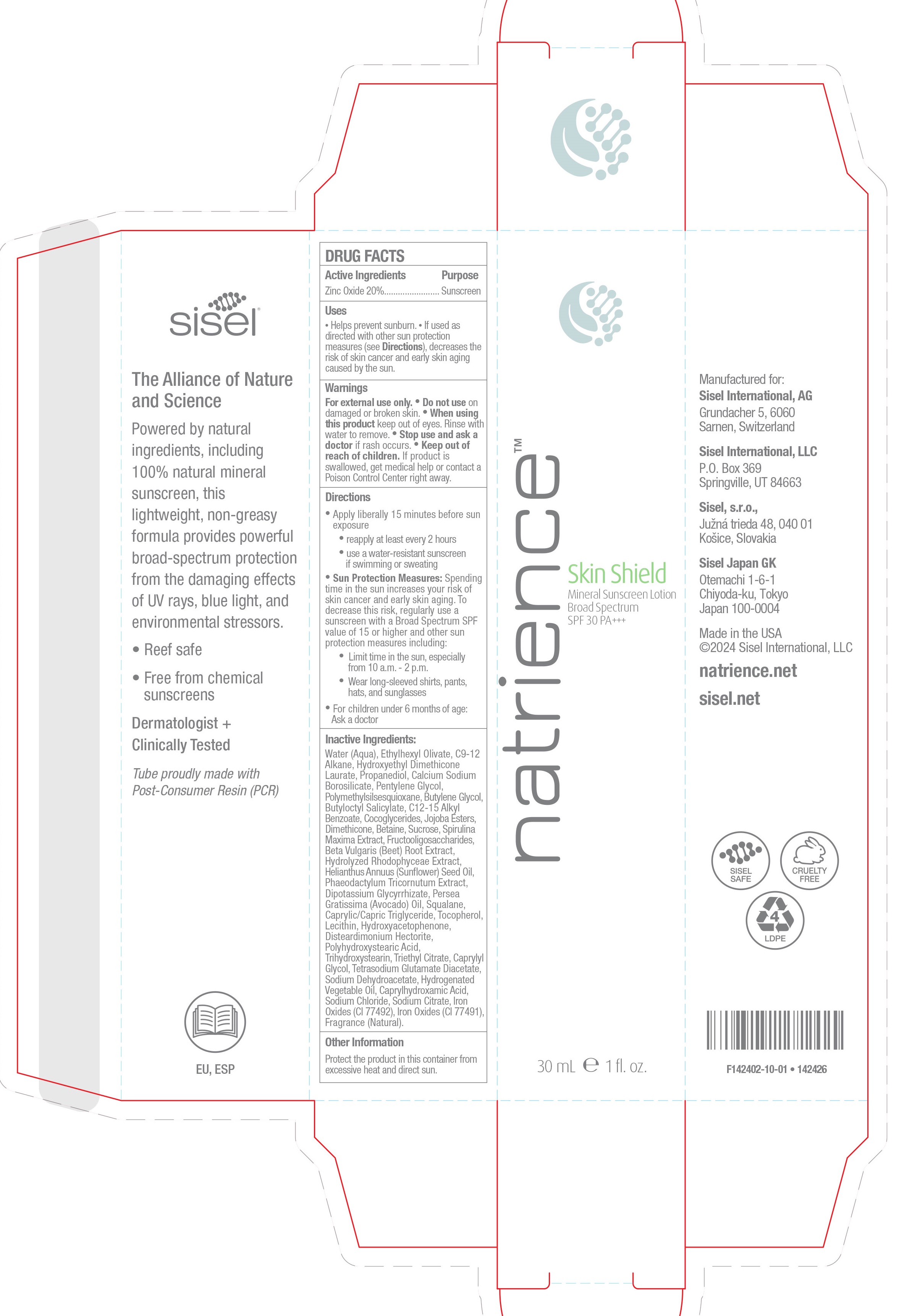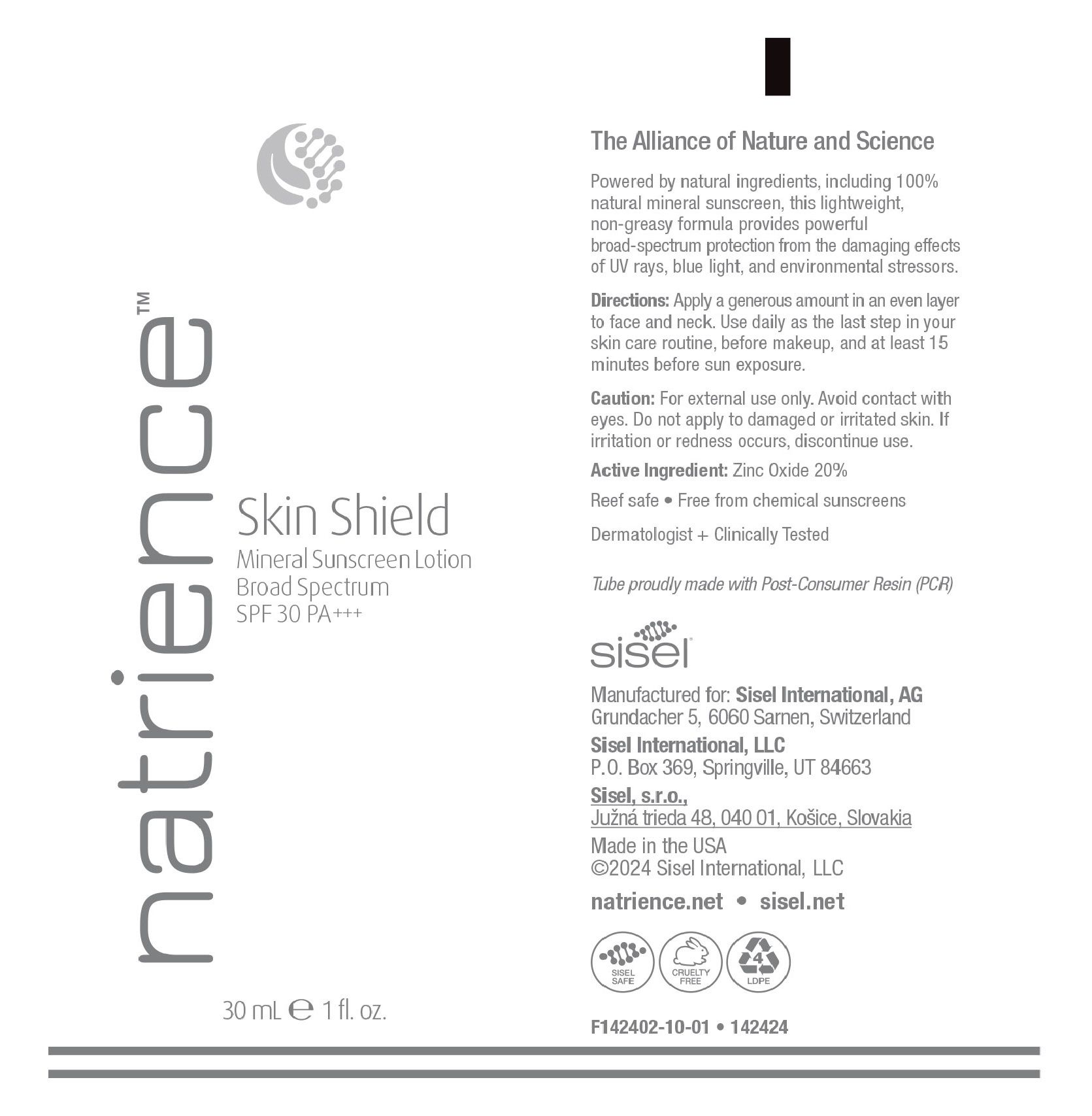 DRUG LABEL: Natrience
NDC: 84352-402 | Form: CREAM
Manufacturer: Sisel International, LLC
Category: otc | Type: HUMAN OTC DRUG LABEL
Date: 20251203

ACTIVE INGREDIENTS: ZINC OXIDE 20 g/100 g
INACTIVE INGREDIENTS: ETHYLHEXYL OLIVATE; COCO-GLYCERIDES; WATER; ALKYL (C12-15) BENZOATE; TOCOPHEROL; SODIUM CITRATE, UNSPECIFIED FORM; C9-12 ALKANE; PENTYLENE GLYCOL; BUTYLENE GLYCOL; AVOCADO OIL; TRIHYDROXYSTEARIN; TRIETHYL CITRATE; SUNFLOWER OIL; PHAEODACTYLUM TRICORNUTUM; DISTEARDIMONIUM HECTORITE; POLYMETHYLSILSESQUIOXANE (4.5 MICRONS); BETA VULGARIS ROOT FRUCTOOLIGOSACCHARIDES; LECITHIN, SOYBEAN; POLYHYDROXYSTEARIC ACID (2300 MW); SPIRULINA MAXIMA; PROPANEDIOL; HYDROGENATED JOJOBA OIL, RANDOMIZED; SQUALANE; HYDROXYACETOPHENONE; CAPRYLHYDROXAMIC ACID; DIMETHICONE; MEDIUM-CHAIN TRIGLYCERIDES; CAPRYLYL GLYCOL; BOROSILICATE GLASS; BUTYLOCTYL SALICYLATE; BETAINE; SUCROSE; SODIUM CHLORIDE; TETRASODIUM GLUTAMATE DIACETATE; SODIUM DEHYDROACETATE; FERRIC OXIDE RED

Active Ingredients

Zinc Oxide 20%........................ Sunscreen

OTC - Purpose

Sunscreen

Indications and Usage

• Apply liberally 15 minutes before sun exposure
• reapply at least every 2 hours
• use a water-resistant sunscreen if swimming or sweating
• Sun Protection Measures: Spending time in the sun increases your risk of skin cancer and early skin aging. To decrease this risk, regularly use a sunscreen with a Broad Spectrum SPF value of 15 or higher and other sun protection measures including:
• Limit time in the sun, especially from 10 a.m. - 2 p.m.
• Wear long-sleeved shirts, pants, hats, and sunglasses
• For children under 6 months of age: Ask a doctor

Dosage and Administration

Cream

Boxed Warnings

For external use only. • Do not use on damaged or broken skin. • When using this product keep out of eyes. Rinse with water to remove. • Stop use and ask a doctor if rash occurs. • Keep out of reach of children. If product is swallowed, get medical help or contact a Poison Control Center right away.

OTC - Keep out of reach of Children

Keep out of reach of children

Inactive Ingredients

Water (Aqua), Ethylhexyl Olivate, C9-12 Alkane, Hydroxyethyl Dimethicone Laurate, Propanediol, Calcium Sodium Borosilicate, Pentylene Glycol, Polymethylsilsesquioxane, Butylene Glycol, Butyloctyl Salicylate, C12-15 Alkyl Benzoate, Cocoglycerides, Jojoba Esters, Dimethicone, Betaine, Sucrose, Spirulina Maxima Extract, Fructooligosaccharides, Beta Vulgaris (Beet) Root Extract,
Hydrolyzed Rhodophyceae Extract, Helianthus Annuus (Sunflower) Seed Oil, Phaeodactylum Tricornutum Extract, Dipotassium Glycyrrhizate, Persea Gratissima (Avocado) Oil, Squalane, Caprylic/Capric Triglyceride, Tocopherol, Lecithin, Hydroxyacetophenone, Disteardimonium Hectorite, Polyhydroxystearic Acid, Trihydroxystearin, Triethyl Citrate, Caprylyl Glycol, Tetrasodium Glutamate Diacetate, Sodium Dehydroacetate, Hydrogenated Vegetable Oil, Caprylhydroxamic Acid, Sodium Chloride, Sodium Citrate, Iron Oxides (CI 77492), Iron Oxides (CI 77491), Fragrance (Natural).

Indications and Usage

Apply a generous amount in an even layer to face and neck. Use daily as the last step in your skin care routine, before makeup, and at least 15 minutes before sun exposure.

Warnings

For external use only. Avoid contact with eyes. Do not apply to damaged or irritated skin. If irritation or redness occurs, discontinue use.

Principal Display

DRUG FACTS
Active Ingredients Purpose
Zinc Oxide 20%........................ Sunscreen
Uses
• Helps prevent sunburn. • If used as
directed with other sun protection
measures (see Directions), decreases the
risk of skin cancer and early skin aging
caused by the sun.
Warnings
For external use only. • Do not use on
damaged or broken skin. • When using
this product keep out of eyes. Rinse with
water to remove. • Stop use and ask a
doctor if rash occurs. • Keep out of
reach of children. If product is
swallowed, get medical help or contact a
Poison Control Center right away.
Directions
• Apply liberally 15 minutes before sun
exposure
• reapply at least every 2 hours
• use a water-resistant sunscreen
if swimming or sweating
• Sun Protection Measures: Spending
time in the sun increases your risk of
skin cancer and early skin aging. To
decrease this risk, regularly use a
sunscreen with a Broad Spectrum SPF
value of 15 or higher and other sun
protection measures including:
• Limit time in the sun, especially
from 10 a.m. - 2 p.m.
• Wear long-sleeved shirts, pants,
hats, and sunglasses
• For children under 6 months of age:
Ask a doctor
Inactive Ingredients:
Water (Aqua), Ethylhexyl Olivate, C9-12
Alkane, Hydroxyethyl Dimethicone
Laurate, Propanediol, Calcium Sodium
Borosilicate, Pentylene Glycol,
Polymethylsilsesquioxane, Butylene Glycol,
Butyloctyl Salicylate, C12-15 Alkyl
Benzoate, Cocoglycerides, Jojoba Esters,
Dimethicone, Betaine, Sucrose, Spirulina
Maxima Extract, Fructooligosaccharides,
Beta Vulgaris (Beet) Root Extract,
Hydrolyzed Rhodophyceae Extract,
Helianthus Annuus (Sunflower) Seed Oil,
Phaeodactylum Tricornutum Extract,
Dipotassium Glycyrrhizate, Persea
Gratissima (Avocado) Oil, Squalane,
Caprylic/Capric Triglyceride, Tocopherol,
Lecithin, Hydroxyacetophenone,
Disteardimonium Hectorite,
Polyhydroxystearic Acid,
Trihydroxystearin, Triethyl Citrate, Caprylyl
Glycol, Tetrasodium Glutamate Diacetate,
Sodium Dehydroacetate, Hydrogenated
Vegetable Oil, Caprylhydroxamic Acid,
Sodium Chloride, Sodium Citrate, Iron
Oxides (CI 77492), Iron Oxides (CI 77491),
Fragrance (Natural).
Other Information
Protect the product in this container from
excessive heat and direct sun.